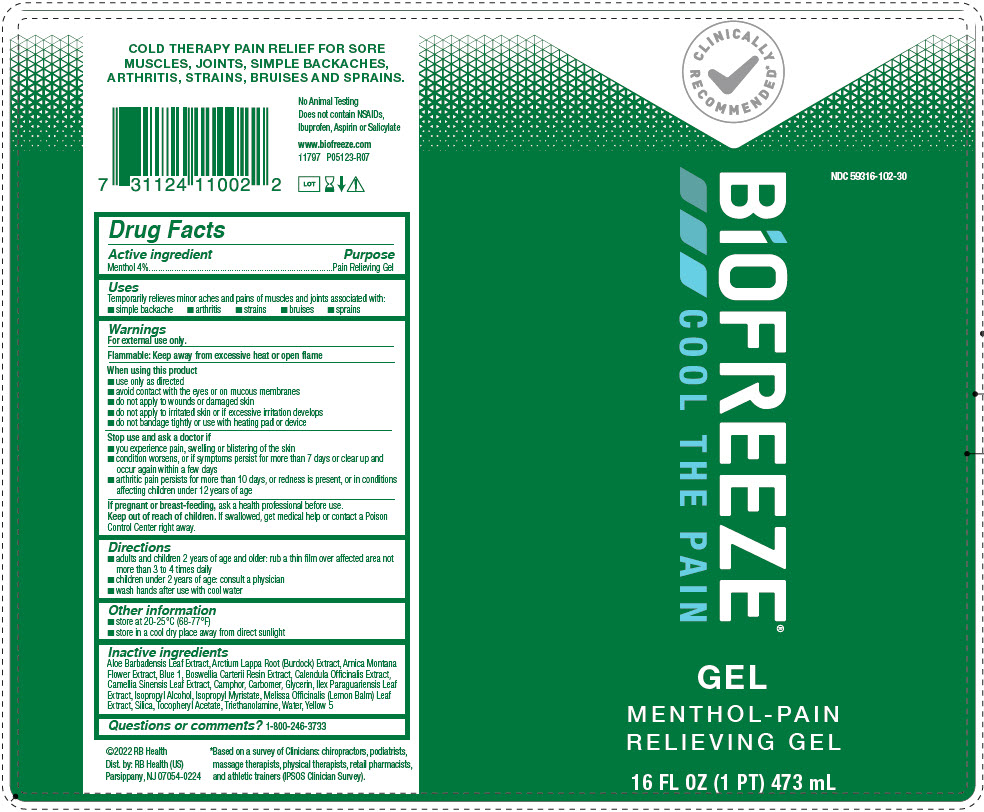 DRUG LABEL: BIOFREEZE
NDC: 59316-102 | Form: GEL
Manufacturer: RB Health (US) LLC
Category: otc | Type: HUMAN OTC DRUG LABEL
Date: 20231113

ACTIVE INGREDIENTS: MENTHOL, UNSPECIFIED FORM 40 mg/1 mL
INACTIVE INGREDIENTS: .ALPHA.-TOCOPHEROL ACETATE; ALOE VERA LEAF; ARNICA MONTANA FLOWER; ARCTIUM LAPPA ROOT; FRANKINCENSE; CALENDULA OFFICINALIS FLOWER; GREEN TEA LEAF; CAMPHOR (SYNTHETIC); GLYCERIN; ILEX PARAGUARIENSIS LEAF; ISOPROPYL ALCOHOL; ISOPROPYL MYRISTATE; MELISSA OFFICINALIS LEAF; SILICON DIOXIDE; TROLAMINE; WATER; FD&C BLUE NO. 1; FD&C YELLOW NO. 5

BiOFREEZE®

Active Ingredients:

Menthol USP 4%

Purpose

Pain Relieving Gel

Uses:

Temporarily relieves minor aches and pains of muscles and joints associated with: • simple backache • arthritis • strains • bruises • sprains

Warnings:

For external use only

Flammable: Keep away from excessive heat or open flame

When using this product:

• Use only as directed • Avoid contact with the eyes or on mucous membranes • Do not apply to wounds or damaged skin • Do not apply to irritated skin or if excessive irritation develops • Do not bandage tightly or use with heating pad or device

Stop use and ask a doctor if:

You experience pain, swelling or blistering of the skin; condition worsens, or if symptoms persist for more than 7 days, or clear up and occur again within a few days; arthritic pain persists for more than 10 days, or redness is present, or in conditions affecting children under 12 years of age

If pregnant or breastfeeding:

Ask a health professional before use

Keep out of reach of children:

If swallowed, get medical help or contact a Poison Control Center right away

Directions:

- Adults and children 2 years of age and older:Rub a thin film over affected area not more than 3 to 4 times daily
- Children under 2 years of age:Consult a physician
- wash hands after use with cool water

Other information

- store at 20-25°C (68-77°F) - store in a cool dry place away from direct sunlight

Inactive Ingredients:

Aloe Barbadensis Leaf Extract, Arctium Lappa Root (Burdock) Extract, Arnica Montana Flower Extract, Blue 1, Boswellia Carterii Resin Extract, Calendula Officinalis Extract, Camellia Sinensis Leaf Extract, Camphor, Carbomer, Glycerin, Ilex Paraguariensis Leaf Extract, Isopropyl Alcohol, Isopropyl Myristate, Melissa Officinalis (Lemon Balm) Leaf Extract, Silica, Tocopheryl Acetate, Triethanolamine, Water, Yellow 5

Questions or Comments:

1-800-246-3733

Dist. by: RB Health (US)
Parsippany, NJ 07054-0224

PRINCIPAL DISPLAY PANEL - 473 mL Bottle Label

CLINICALLY
RECOMMENDED®

NDC 59316-102-30

BiOFREEZE®
COOL THE PAIN

GEL

MENTHOL-PAIN
RELIEVING GEL

16 FL OZ (1 PT) 473 mL